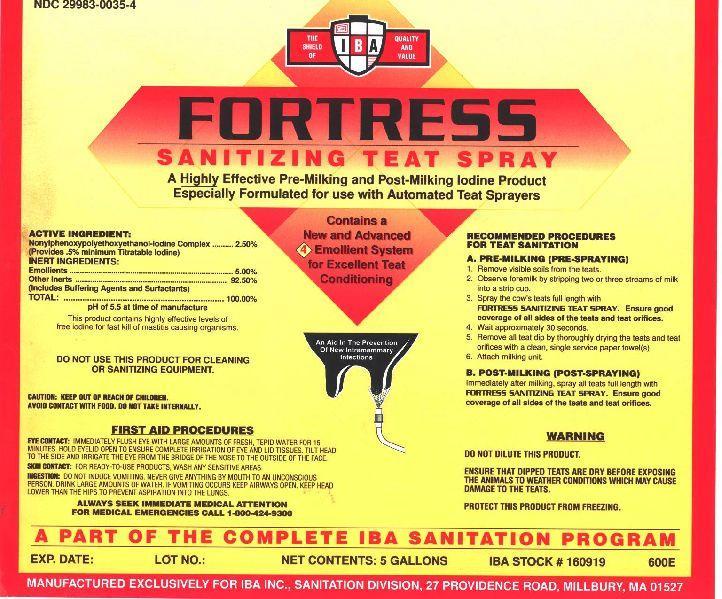 DRUG LABEL: FORTRESS S PRAY
NDC: 29983-0035 | Form: SOLUTION
Manufacturer: IBA
Category: animal | Type: OTC ANIMAL DRUG LABEL
Date: 20220719

ACTIVE INGREDIENTS: IODINE 5 g/1 L

FORTRESS SANITIZING TEAT SPRAY A HIGHLY EFFECT PRE-MILKING AND POST-MILKING IODINE PRODUCT ESPECIALLY FORMULATED FOR USE WITH AUTOMATED TEAT SPRAYERS CONTAINS A NEW AND ADVANCED 4 EMOLLIENT SYSTEM FOR EXCELLENT TEAT CONDITIONING

ACTIVE INGREDIENT:

Nonylphenoxypolyethoxyethanol -Iodine Complex.....2.50%
(Provides .5% minimum Titratable Iodine)
INERT INGREDIENTS
Emollients.......5.00%
Other Inerts.....92.50%
(Includes Buffering Agents and Surfactants)
Total.................100%
pH of 5.5 at time of manufacture

This product contains highly effect levels of free iodine for fast kill of mastitis causing organisms.

INDICATIONS AND USAGE

RECOMMENDED PROCEDURES FOR TEAT SANITATION
A. PRE-MILKING (PRE-SPRAYING)
1. REMOVE VISIBLE SOILS FROM THE TEATS.
2. OBSERVE FOREMILK BY STRIPPING TWO OR THREE STREAMS OF MILK INTO A STRIP CUP.
3. SPRAY THE COW'S TEATS FULL LENGTH WITH FORTRESS SANITIZING TEAT SPRAY .
4. WAIT APPROXIMATELY 30 SECONDS.
5. REMOVE ALL TEAT DIP BY THOROUGHLY DRYING THE TEATS AND TEAT ORIFICES WITH A CLEAN, SINGLE SERVICE PAPER TOWEL(S).
6. ATTACH MILKING UNIT.
B. POST-MILKING (POST-DIPPING)
Immediately after milking, spray all teats full length with FORTRESS SANITIZING TEAT SPRAY Teat Dip. Ensure good coverage of all sides of the teats and teat orifices.

A PART OF THE COMPLETE IBA SANITATION PROGRAM

WARNINGS AND PRECAUTIONS SECTION

DO NOT DILUTE THIS PRODUCT

ENSURE THAT DIPPED TEATS ARE DRY BEFORE EXPOSING THE ANIMALS TO WEATHER CONDITIONS WHICH MAY CAUSE DAMAGE TO THE TEATS.
PROTECT THIS PRODUCT FROM FREEZING.

DO NOT USE THIS PRODUCT FOR CLEANING OR SANITIZING EQUIPMENT.

CAUTION: KEEP OUT OF REACH OF CHILDREN.
AVOID CONTACT WITH FOOD. DO NOT TAKE INTERNALLY.

EYE CONTACT: IMMEDIATELY FLUSH EYE WITH LARGE AMOUNTS OF FRESH, TEPID WATER FOR 15 MINUTES. HOLD EYELID OPEN TO ENSURE COMPLETE IRRIGATION OF EYE AND LID TISSUES. TILT HEAD TO THE SIDE AND IRRIGATE THE EYE FROM THE BRIDGE OF THE NOSE TO THE OUTSIDE OF THE FACE.
SKIN CONTACT: FOR READY-TO-USE, WASH ANY SENSITIVE AREAS.
INGESTION: DO NOT INDUCE VOMITING. NEVER GIVE ANYTHING BY MOUTH TO AN UNCONSCIOUS PERSON. DRINK LARGE AMOUNTS OF WATER. IF VOMITING OCCURS KEEP AIRWAYS OPEN. KEEP HEAD LOWER THAN THE HIPS TO PREVENT ASPIRATION INTO THE LUNGS.

ALWAYS SEEK IMMEDIATE MEDICAL ATTENTION

FOR MEDICAL EMERGENCIES CALL 1-800-424-9300